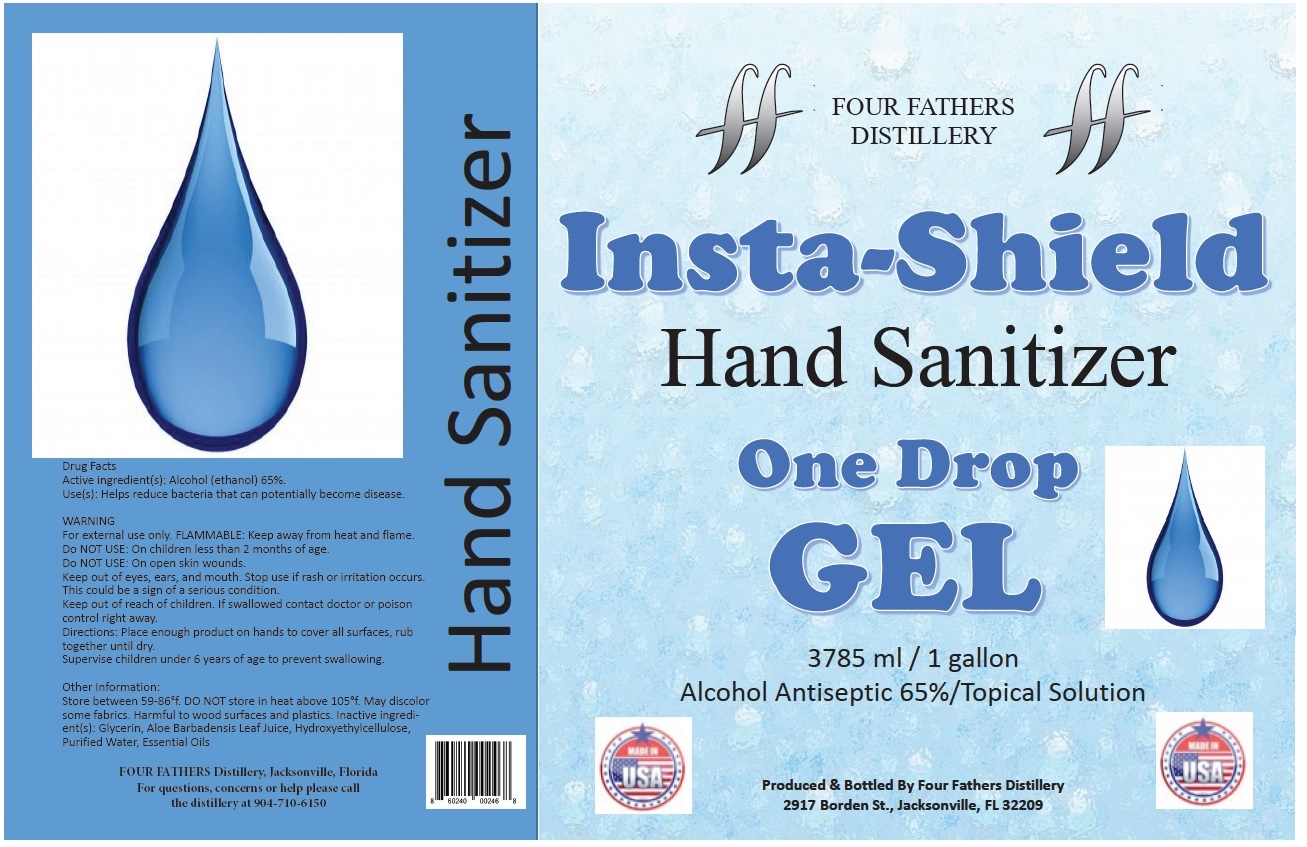 DRUG LABEL: Insta-Shield
NDC: 78829-101 | Form: GEL
Manufacturer: Four Fathers Distillery LLC
Category: otc | Type: HUMAN OTC DRUG LABEL
Date: 20201008

ACTIVE INGREDIENTS: ALCOHOL 65 mL/100 mL
INACTIVE INGREDIENTS: GLYCERIN; ALOE VERA LEAF; HYDROXYETHYL CELLULOSE, UNSPECIFIED; WATER; LAVENDER OIL; EUCALYPTUS OIL; WEST INDIAN LEMONGRASS OIL

Insta-Shield Hand Sanitizer Gel

Active ingredient(s):

Alcohol (ethanol) 65%.

Purpose

Antiseptic

Use(s):

Helps reduce bacteria that can potentially become disease.

WARNING

For external use only. FLAMMABLE: Keep away from heat and flame.
Do NOT USE: On children less than 2 months of age.
Do NOT USE: On open skin wounds.
Keep out of eyes, ears, and mouth. Stop use if rash or irritation occurs. This could be a sign of a serious condition.

Keep out of reach of children. If swallowed contact doctor or poison control right away.

Directions:

Place enough product on hands to cover all surfaces, rub together until dry.
Supervise children under 6 years of age to prevent swallowing.

Other Information:

Store between 59-86°F. DO NOT store in heat above 105°F. May discolor some fabrics. Harmful to wood surfaces and plastics.

Inactive ingredient(s):

Glycerin, Aloe Barbadensis Leaf Juice, Hydroxyethylcellulose, Purified Water, Essential Oils

One Drop GEL

Alcohol Antiseptic 65%/Topical Solution

Produced & Bottled By Four Fathers Distillery
2917 Borden St., Jacksonville, FL 32209

MADE IN USA

FOUR FATHERS Distillery, Jacksonville, Florida
For questions, concerns or help please call the distillery at 904-710-615